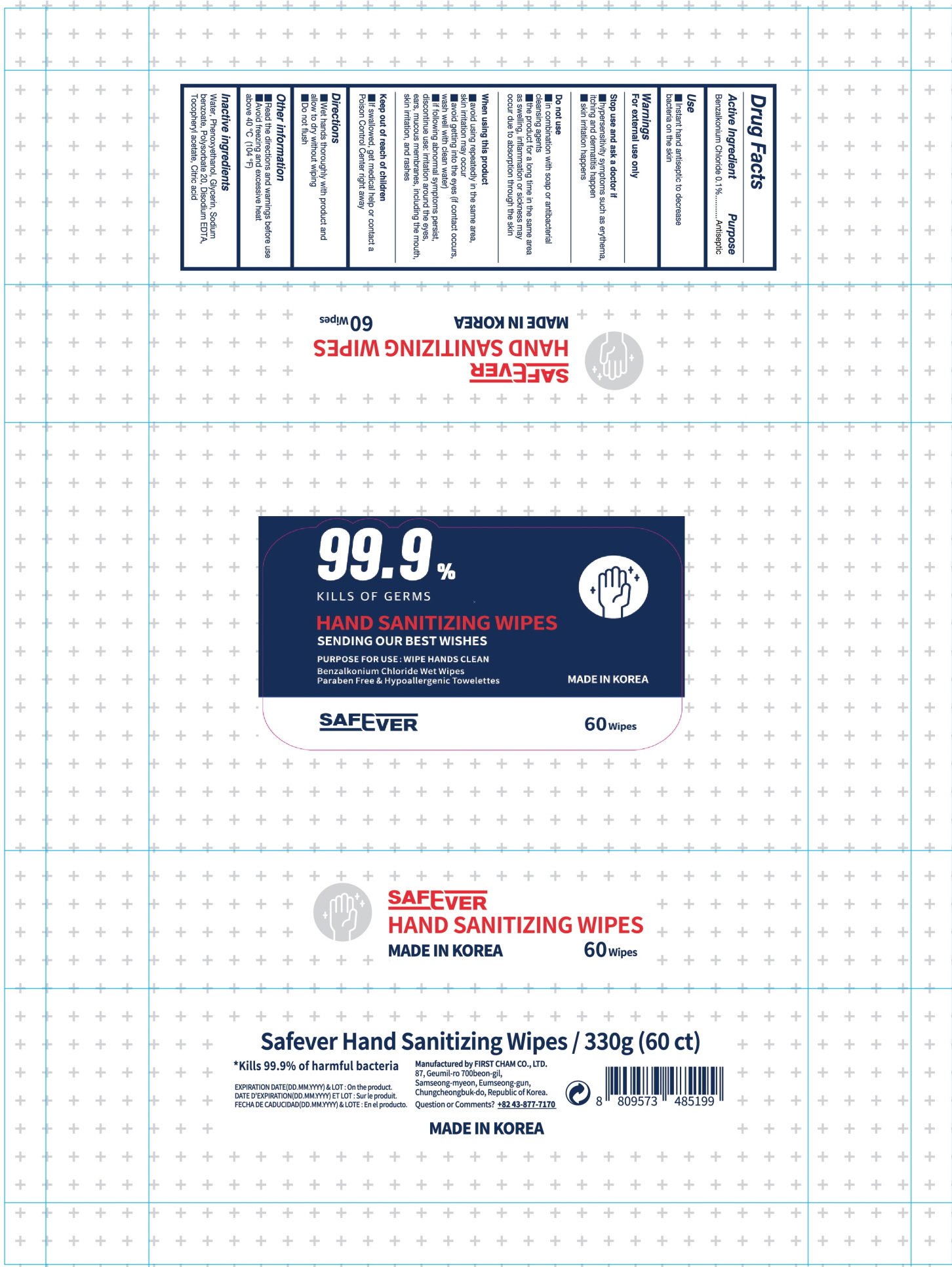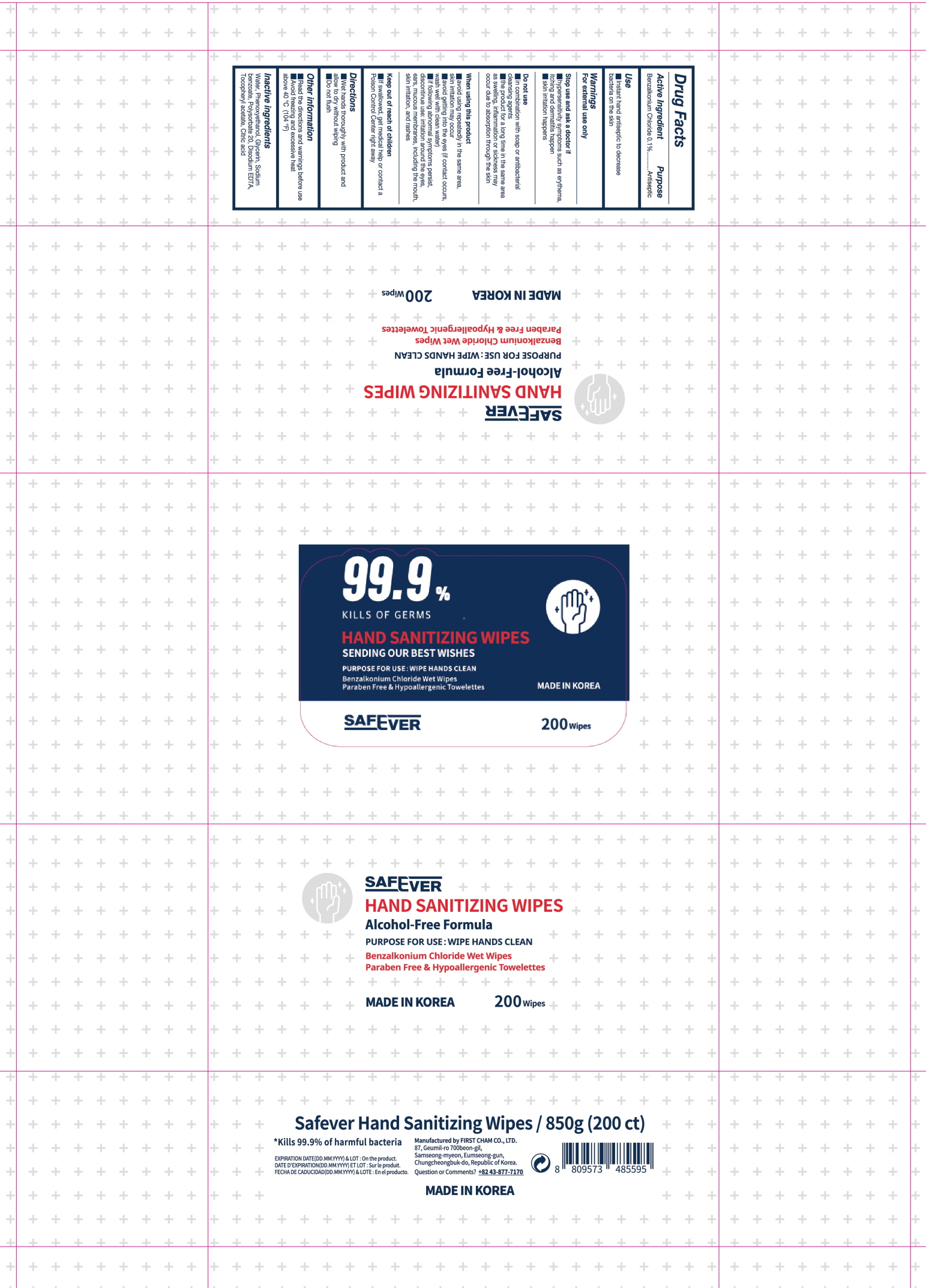 DRUG LABEL: Safever Hand Sanitizing Wipes
NDC: 73923-0140 | Form: LIQUID
Manufacturer: FIRSTCHAM CO., LTD
Category: otc | Type: HUMAN OTC DRUG LABEL
Date: 20201013

ACTIVE INGREDIENTS: BENZALKONIUM CHLORIDE 0.1 g/100 g
INACTIVE INGREDIENTS: WATER; PHENOXYETHANOL; GLYCERIN; SODIUM BENZOATE; Polysorbate 20; EDETATE DISODIUM ANHYDROUS; .ALPHA.-TOCOPHEROL ACETATE; CITRIC ACID MONOHYDRATE

Drug Facts

ACTIVE INGREDIENT

Benzalkonium Chloride 0.1%

INACTIVE INGREDIENTS

Water, Phenoxyethanol, Glycerin, Sodium benzoate, Polysorbate 20, Disodium EDTA, Tocopheryl acetate, Citric acid

PURPOSE

Antiseptic

WARNINGS

For external use only

Stop use and ask a doctor if
■ hypersensitivity symptoms such as erythema, itching and dermatitis happen
■ skin irritation happens

Do not use
■ in combination with soap or antibacterial cleansing agents
■ the product for a long time in the same area as swelling, inflammation or sickness may occur due to absorption through the skin

When using this product
■ avoid using repeatedly in the same area, skin irritation may occur
■ avoid getting into the eyes (if contact occurs, wash well with clean water)
■ if following abnormal symptoms persist, discontinue use: irritation around the eyes, ears, mucous membranes, including the mouth, skin irritation, and rashes

KEEP OUT OF REACH OF CHILDREN

■ If swallowed, get medical help or contact a Poison Control Center right away

Use

■ Instant hand antiseptic to decrease bacteria on the skin

Directions

■ Wet hands thoroughly with product and allow to dry without wiping

■ Do not flush

Other information

■ Read the directions and warnings before use

■ Avoid freezing and excessive heat above 40 ℃ (104 ℉)